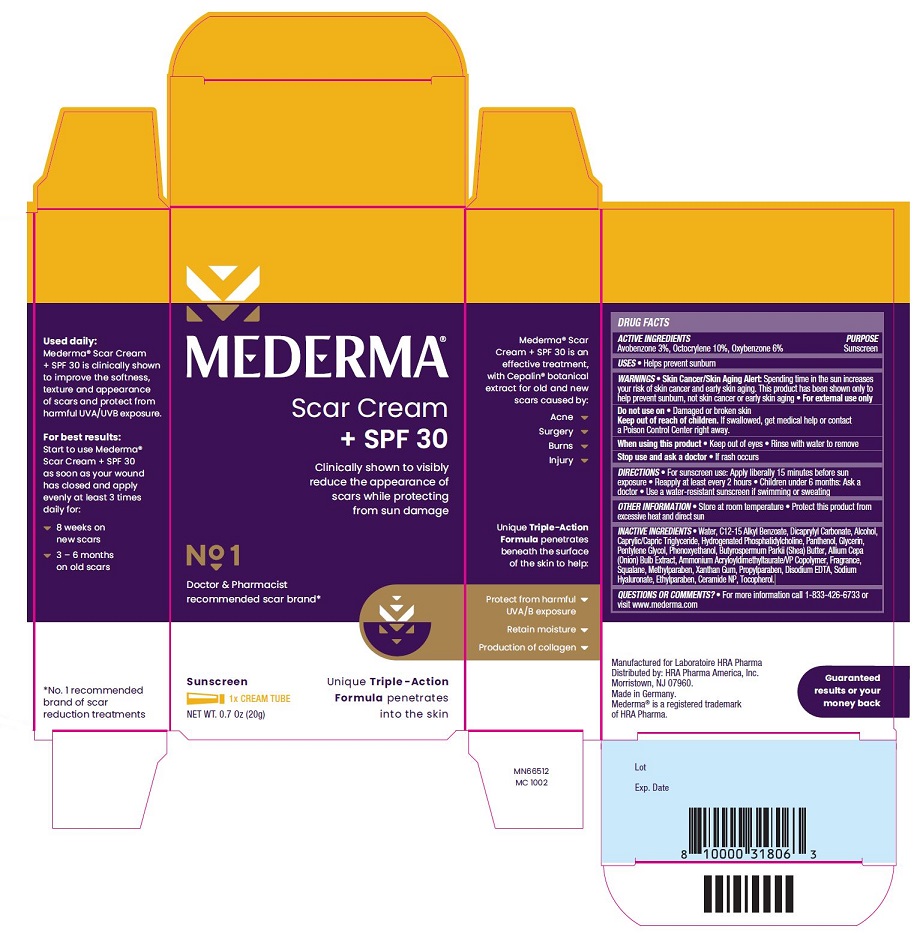 DRUG LABEL: Mederma Scar Cream
NDC: 73302-205 | Form: CREAM
Manufacturer: HRA PHARMA AMERICA, INC.
Category: otc | Type: HUMAN OTC DRUG LABEL
Date: 20250127

ACTIVE INGREDIENTS: AVOBENZONE 30 mg/1 g; OCTOCRYLENE 100 mg/1 g; OXYBENZONE 60 mg/1 g
INACTIVE INGREDIENTS: Water; ALKYL (C12-15) BENZOATE; DICAPRYLYL CARBONATE; ALCOHOL; MEDIUM-CHAIN TRIGLYCERIDES; HYDROGENATED SOYBEAN LECITHIN; PANTHENOL; GLYCERIN; PENTYLENE GLYCOL; PHENOXYETHANOL; SHEA BUTTER; ONION; AMMONIUM ACRYLOYLDIMETHYLTAURATE/VP COPOLYMER; SQUALANE; METHYLPARABEN; XANTHAN GUM; PROPYLPARABEN; Edetate Disodium Anhydrous; HYALURONATE SODIUM; ETHYLPARABEN; CERAMIDE NP; Tocopherol

MEDERMA® Drug Facts

Active Ingredients

Avobenzone 3%

Octocrylene 10%

Oxybenzone 6%

Purpose

Sunscreen

Uses

- Helps prevent sunburn

Warnings

- Skin Cancer/Skin Aging Alert: Spending time in the sun increases your risk of skin cancer and early skin aging. This product has been shown only to help prevent sunburn, not skin cancer or early skin aging.
- For external use only

Do not use on

- Damaged or broken skin

Keep out of reach of children.

If swallowed, get medical help or contact a Poison Control Center right away.

When using this product

- Keep out of eyes
- Rinse with water to remove

Stop use and ask a doctor

- If rash occurs

Directions

- For sunscreen use: Apply liberally 15 minutes before sun exposure
- Reapply at least every 2 hours
- Children under 6 months: Ask a doctor
- Use a water-resistant sunscreen if swimming or sweating

Other Information

- Store at room temperature
- Protect this product from excessive heat and direct sun

Inactive Ingredients

- Water, C12-15 Alkyl Benzoate, Dicaprylyl Carbonate, Alcohol, Caprylic/Capric Triglyceride, Hydrogenated Phosphatidylcholine, Panthenol, Glycerin, Pentylene Glycol, Phenoxyethanol, Butyrospermum Parkii (Shea) Butter, Allium Cepa (Onion) Bulb Extract, Ammonium Acryloyldimethyltaurate/VP Copolymer, Fragrance, Squalane, Methylparaben, Xanthan Gum, Propylparaben, Disodium EDTA, Sodium Hyaluronate, Ethylparaben, Ceramide NP, Tocopherol.

Questions or Comments

- For more information call 1-833-426-6733 or visit www.mederma.com

PACKAGE LABEL.PRINCIPAL DISPLAY PANEL

MEDERMA®
Scar Cream + SPF 30
Clinically shown to visibly reduce the appearance of scars while protecting from sun damage
No. 1 Doctor & Pharmacist recommended scar brand
Sunscreen
1 x CREAM TUBE
NET WT. 0.7 0z (20g)
Unique Triple-Action Formula penetrates into the skin